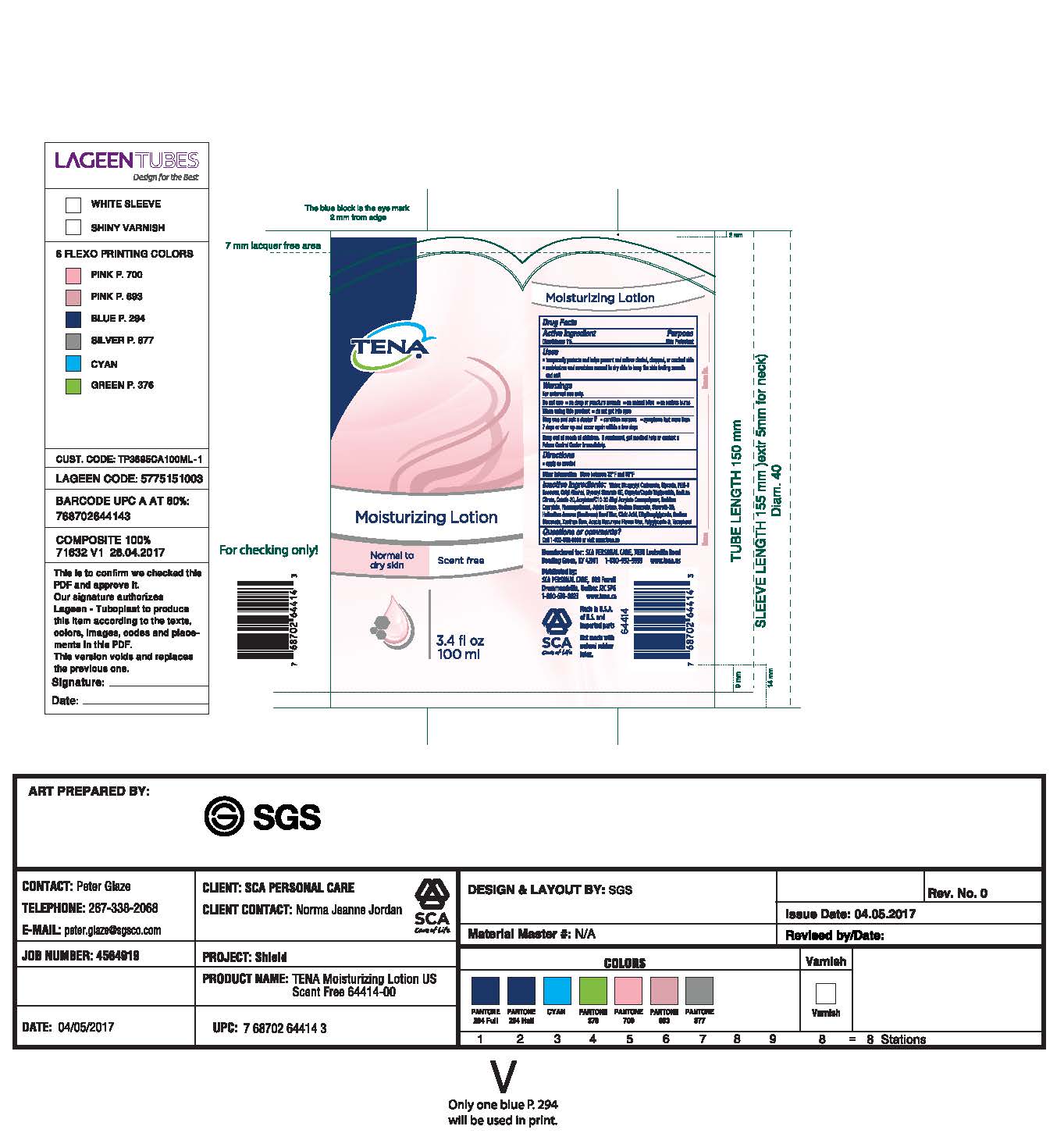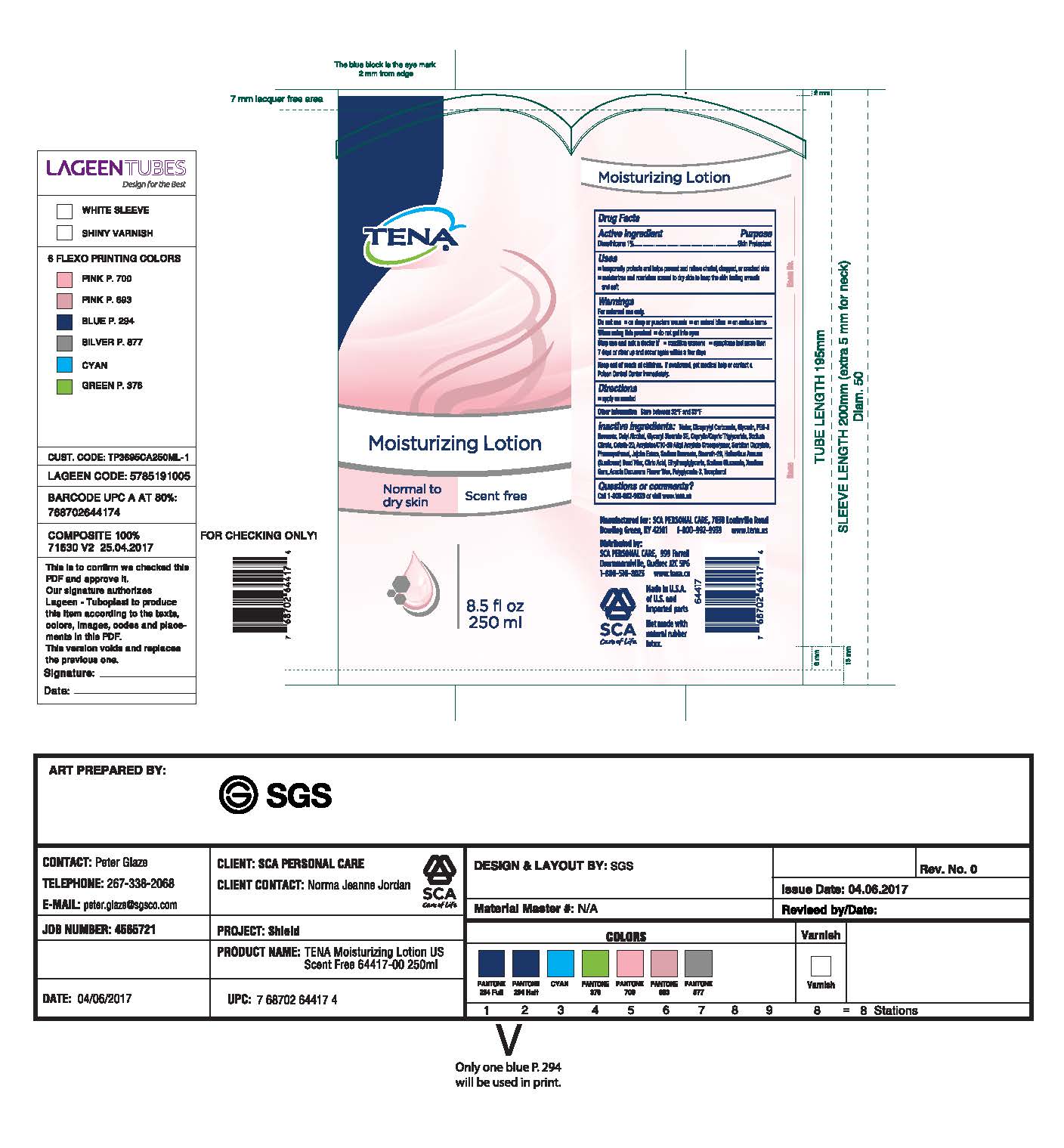 DRUG LABEL: TENA
NDC: 59608-002 | Form: CREAM
Manufacturer: SCA Personal Care Inc.
Category: otc | Type: HUMAN OTC DRUG LABEL
Date: 20170718

ACTIVE INGREDIENTS: DIMETHICONE .01 g/100 mL
INACTIVE INGREDIENTS: WATER; DICAPRYLYL CARBONATE; GLYCERIN; YELLOW WAX; CETYL ALCOHOL; GLYCERYL STEARATE SE; MEDIUM-CHAIN TRIGLYCERIDES; SODIUM CITRATE; CETETH-20; CARBOMER INTERPOLYMER TYPE A (ALLYL SUCROSE CROSSLINKED); SORBITAN; PHENOXYETHANOL; JOJOBA OIL, RANDOMIZED; SODIUM BENZOATE; STEARETH-20; HELIANTHUS ANNUUS SEED WAX; CITRIC ACID MONOHYDRATE; ETHYLHEXYLGLYCERIN; SODIUM GLUCONATE; XANTHAN GUM; ACACIA DECURRENS FLOWER WAX; POLYGLYCERIN-3; TOCOPHEROL

Drug Facts

Active Ingredient

Dimethicone 1%

Purpose

Skin Protectant

Uses

•temporarily protects and helps prevent and relieve chafed, chapped, or cracked skin

•moisturizes and nourishes normal to dry skin to keep the skin feeling smooth and soft

Warnings

For external use only.

Do not use •on deep or puncture wounds •on animal bites •on serious burns

When using this product •do not get into eyes

Stop use and ask a doctor if •condition worsens •symptoms last more than

7 days or clear up and occur again within a few days

Keep out of reach of children. If swallowed, get medical help or contact a

Poison Control Center immediately.

Directions

•apply as needed

Other information Store between 32° F and 85° F

Inactive Ingredients: Water, Dicaprylyl Carbonate, Glycerin, PEG-8

Beeswax, Cetyl Alcohol, Glyceryl Stearate SE, Caprylic/Capric Triglyceride, Sodium

Citrate, Ceteth-20, Acrylates/C10-30 Alkyl Acrylate Crosspolymer, Sorbitan

Caprylate, Phenoxyethanol, Jojoba Esters, Sodium Benzoate, Steareth-20,

Helianthus Annus (Sunflower) Seed Wax, Citric Acid, Ethylhexylglycerin, Sodium

Gluconate, Xantham Gum, Acacia Decurrens Flower Wax, Polyglycerin-3, Tocopherol

Questions or comments?

Call 1-800-992-9939 or visit www.tena.us